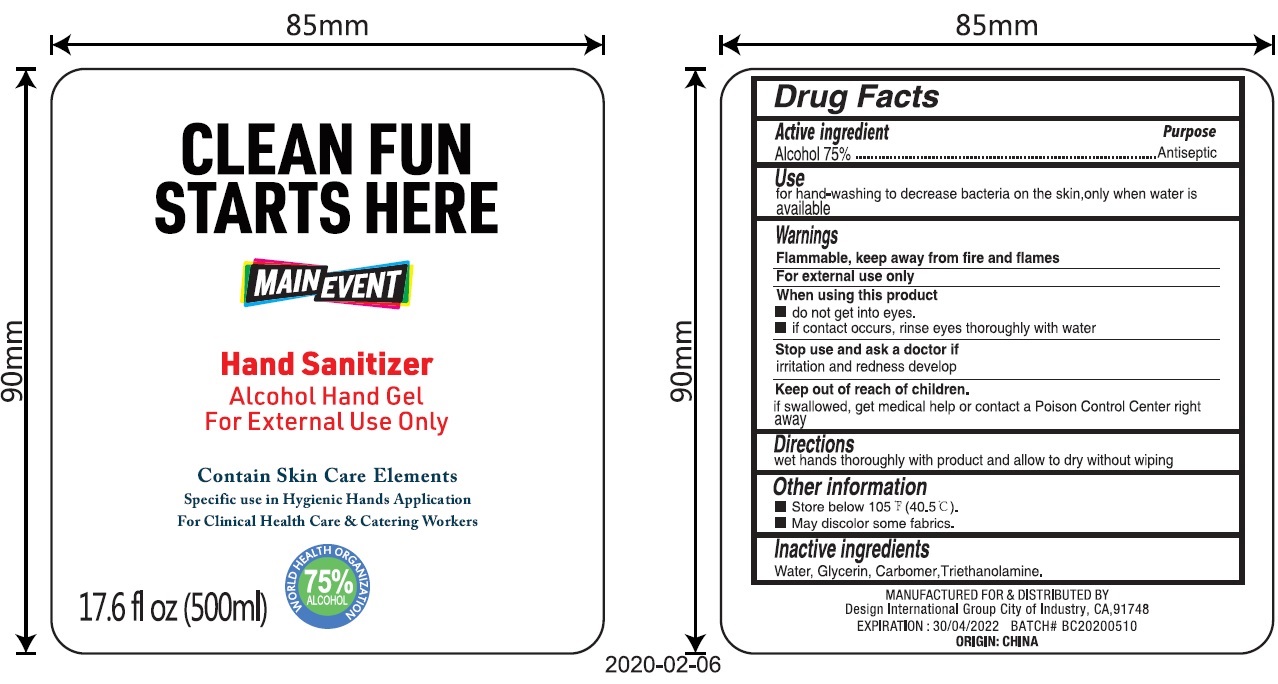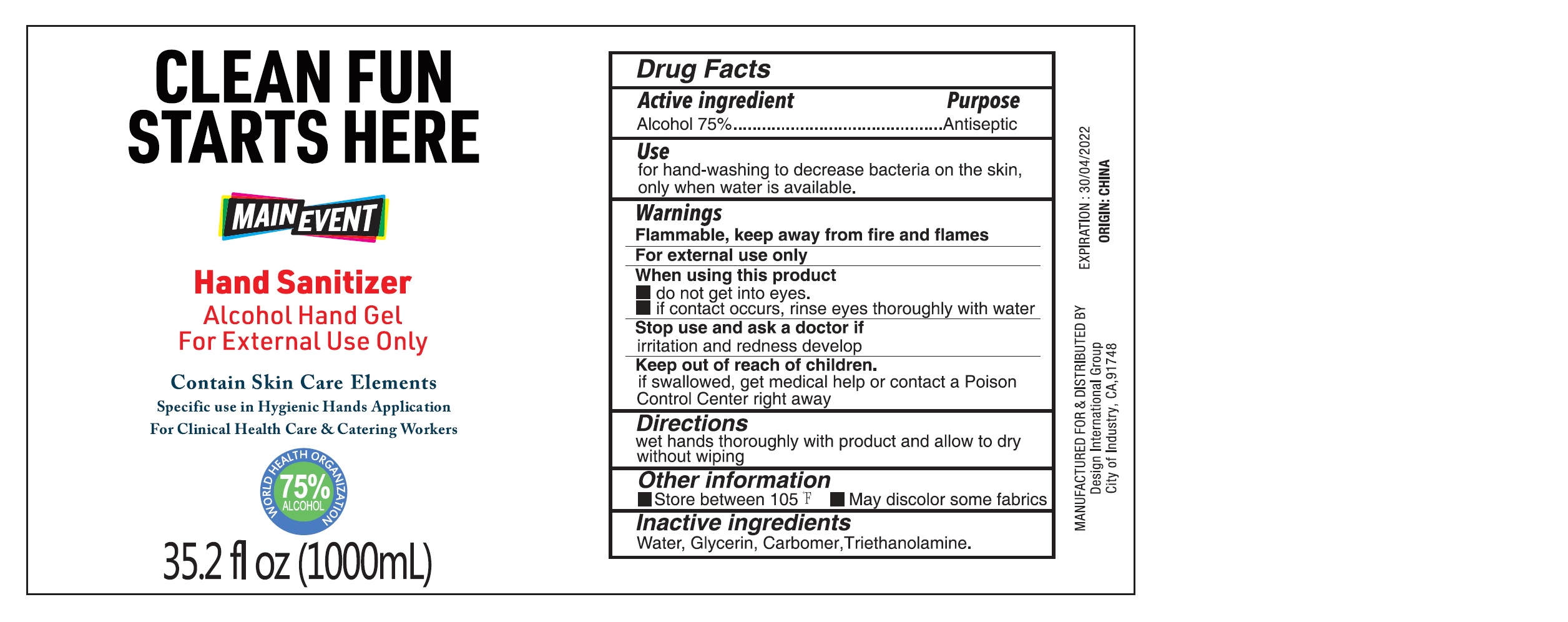 DRUG LABEL: Hand Sanitizer Alcohol Hand
NDC: 76892-001 | Form: GEL
Manufacturer: Design International Group
Category: otc | Type: HUMAN OTC DRUG LABEL
Date: 20231026

ACTIVE INGREDIENTS: ALCOHOL 0.75 mL/1 mL
INACTIVE INGREDIENTS: WATER; GLYCERIN; CARBOMER HOMOPOLYMER, UNSPECIFIED TYPE; TROLAMINE

Hand Sanitizer(Alcohol Hand Gel)

Active ingredient

Alcohol 75%

Purpose

Antiseptic

Use

for hand-washing to decrease bacteria on the skin,only when water is available

Warnings

Flammable, keep away from fire and flames

For external use only

When using this product

- do not get into eyes.
- if contact occurs, rinse eyes thoroughly with water

Stop use and ask a doctor if

- irritation and redness develop

Keep out of reach of childre.

- if swallowed, get medical help or contact a Poison Control Center right away

Directions

- wet hands thoroughly with product and allow to dry without wiping

Inactive ingredients

Water, Glycerin, Carbomer,Triethanolamine.